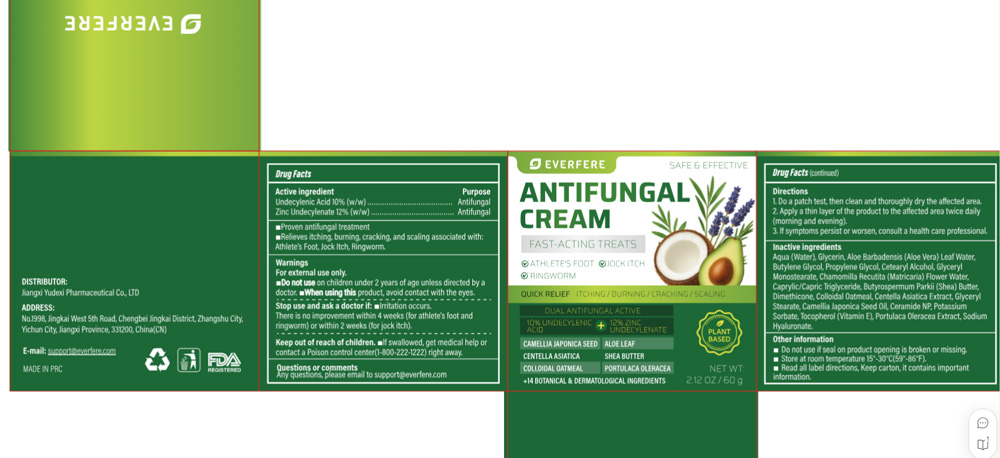 DRUG LABEL: EVERFERE ANTIFUNGAL
NDC: 85248-146 | Form: CREAM
Manufacturer: Jiangxi Yudexi Pharmaceutical Co., LTD
Category: otc | Type: HUMAN OTC DRUG LABEL
Date: 20260227

ACTIVE INGREDIENTS: ZINC UNDECYLENATE 12 g/100 g; UNDECYLENIC ACID 10 g/100 g
INACTIVE INGREDIENTS: GLYCERIN; SODIUM HYALURONATE; PROPYLENE GLYCOL; DIMETHICONE; GLYCERYL MONOSTEARATE; CHAMOMILE FLOWER OIL; TOCOPHEROL; CAMELLIA JAPONICA SEED OIL; CENTELLA ASIATICA TRITERPENOIDS; BUTYLENE GLYCOL; CAPRYLIC/CAPRIC TRIGLYCERIDE; BUTYROSPERMUM PARKII (SHEA) BUTTER; OATMEAL; POTASSIUM SORBATE; CETOSTEARYL ALCOHOL; ALOE VERA LEAF; CERAMIDE NP; PURSLANE; WATER

85246-146

Active Ingredient

Undecylenic Acid 10% (w/w) Zinc Undecylenate 12%(w/w）

Purpose

Antifungal

Use

■Proven antifungal treatment
■Relieves itching, burning, cracking, and scaling associated with:Athlete's Foot, Jock Itch, Ringworm.

Warnings

For external use only.

■Do not use on children under 2 years of age unless directed by a doctor.

When Using

■When using this product, avoid contact with the eyes.

Stop Use

■Irritation occurs. There is no improvement within 4 weeks (for athlete's foot and ringworm) or within 2 weeks (for jock itch).

Ask Doctor

■Irritation occurs.
There is no improvement within 4 weeks (for athlete's foot and ringworm) or within 2 weeks (for jock itch).

Keep Oot Of Reach Of Children

■If swallowed, get medical help or contact a Poison control center (1-800-222-1222) right away.

Directions

1.Do a patch test, then clean and thoroughly dry the affected area.
2.Apply a thin layer of the product to the affected area twice daily (morning and evening).
3.If symptoms persist or worsen, consult a health care professional.

Other information

■ Do not use if seal on product opening is broken or missing.
■ Store at room temperature 15°-30°C (59°-86°F).
■ Read all label directions. Keep carton, it contains important information.

Inactive ingredients

Aqua (Water), Glycerin, Aloe Barbadensis (Aloe Vera) Leaf Water, Butylene Glycol, Propylene Glycol, Cetearyl Alcohol, Glyceryl Monostearate, Chamomilla Recutita (Matricaria) Flower Water, Caprylic/Capric Triglyceride, Butyrospermum Parkii (Shea) Butter, Dimethicone, Colloidal Oatmeal, Centella Asiatica Extract, Glyceryl Stearate, Camellia Japonica Seed Oil, Ceramide NP, Potassium Sorbate, Tocopherol (Vitamin E), Portulaca Oleracea Extract, Sodium Hyaluronate.